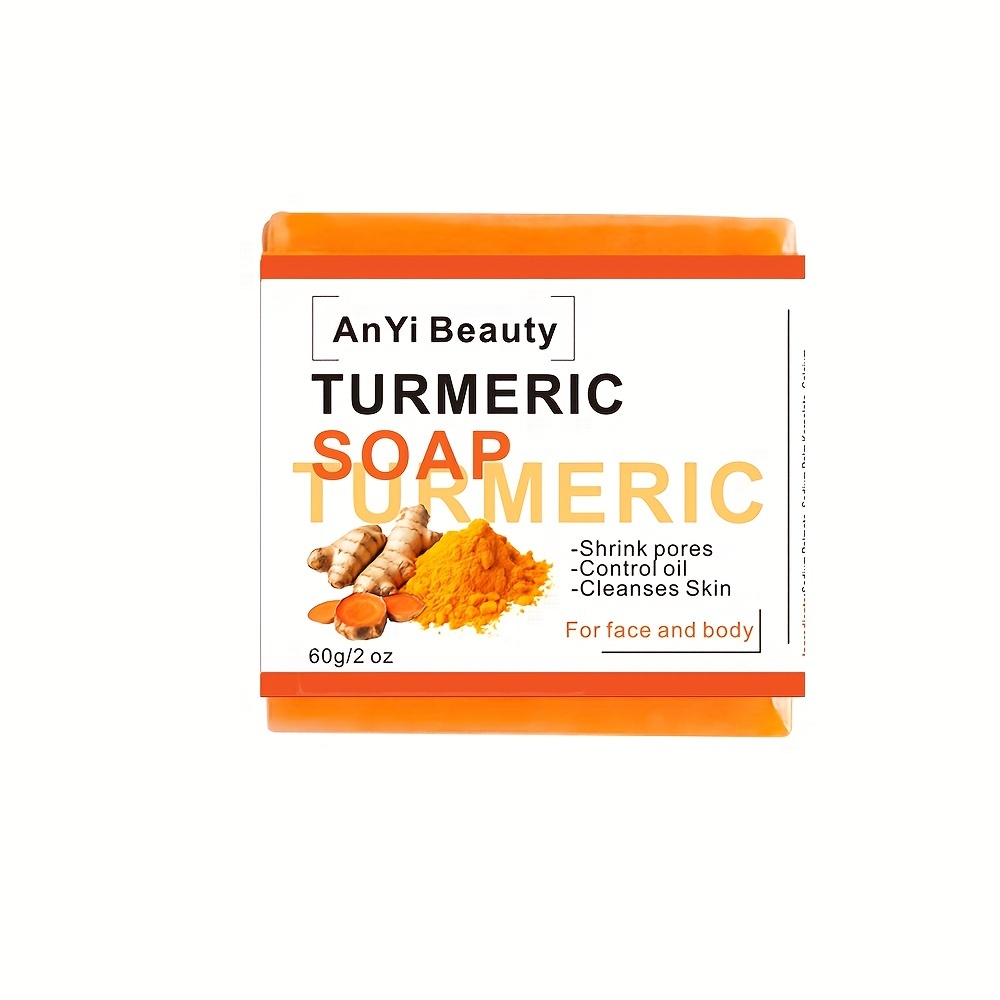 DRUG LABEL: AnYi Beauty TurmericSoap
NDC: 84037-0097 | Form: SOAP
Manufacturer: Guangzhou Zhicunxiu Cosmetics Co., Ltd
Category: otc | Type: HUMAN OTC DRUG LABEL
Date: 20240531

ACTIVE INGREDIENTS: SALICYLIC ACID 5 mg/1 g
INACTIVE INGREDIENTS: CALCIUM CARBONATE; SODIUM PALMATE; COCAMIDOPROPYL BETAINE; SODIUM PALM KERNELATE; WATER

AnYi Beauty TurmericSoap

Active Ingredients

Salicylic acid 0.5%

Purpose

Acne treatment

Uses

treats and helps prevent acne

Warnings

For external use only.Avoid direct contact with eyes.

Do not useon open wounds, eczema and dermatitis.
Stop usingif red spots, swelling, itching or irritation occurs.

Keep out of reach of children.

lf pregnant or breast-feeding,ask a healthcare professional before use. lf accidental ingestion and adverse reaction occurs, get medical help or contact a Poison Control Center.

Directions

- Lather onto wet skin and massage for 12 minutes.
- Rinse throughly For best result, use it regularly.

Other Information

store in a cool dry place, away from direct sunlight.

Inactive Ingredients

Sodium Palmate, Sodium Palm Kernelate, Calcium Carbonate, Curcuma Longa Root, Propolis Extract, Hydrogenated Olive Oil, Tocopherylacetate, Aqua, Cocamidopropyl Betaine, Disodium EDTA, BHT, Disodium Distvrylbiphenyl Disulfonate, CI 19140, CI 16255, CI 15985, CI 16185, Parfum

Questions?

Email-us zcunxiu@163.com